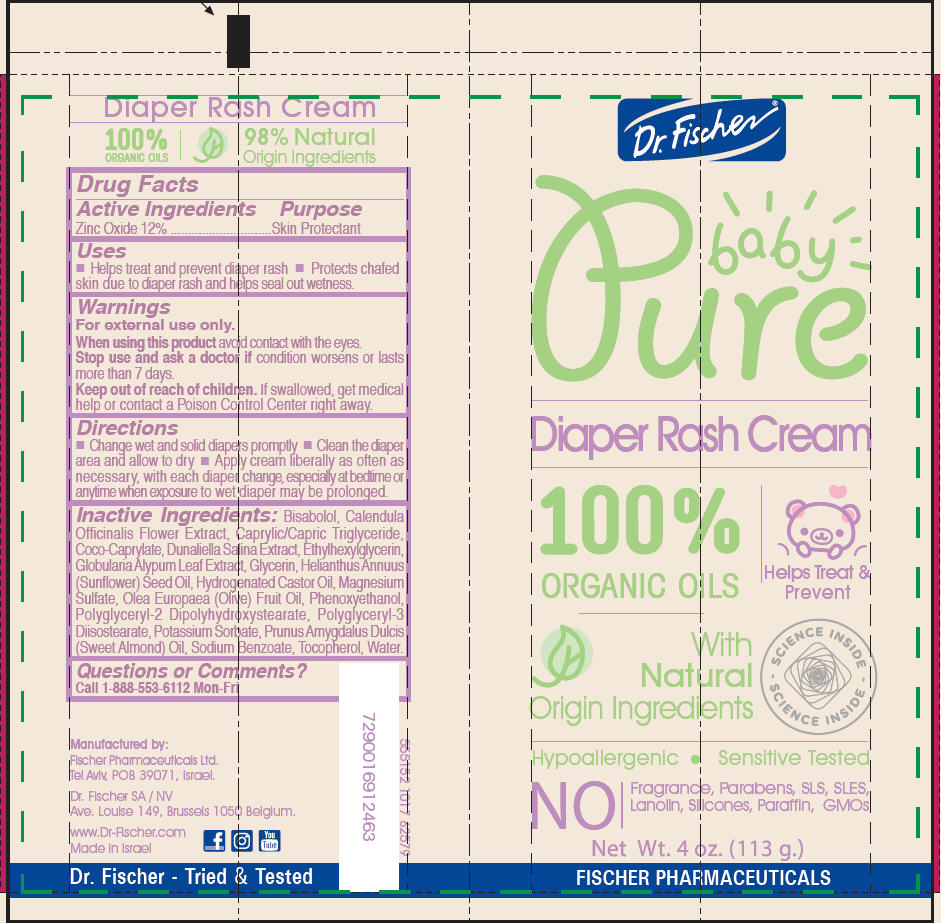 DRUG LABEL: Pure Baby Diaper Rash
NDC: 59886-414 | Form: CREAM
Manufacturer: Fischer Pharmaceuticals Ltd
Category: otc | Type: HUMAN OTC DRUG LABEL
Date: 20171228

ACTIVE INGREDIENTS: Zinc Oxide 40 g/100 g
INACTIVE INGREDIENTS: LEVOMENOL; CALENDULA OFFICINALIS FLOWER; MEDIUM-CHAIN TRIGLYCERIDES; Coco-Caprylate; DUNALIELLA SALINA; Ethylhexylglycerin; GLOBULARIA CORDIFOLIA WHOLE; Glycerin; SUNFLOWER OIL; Hydrogenated Castor Oil; MAGNESIUM SULFATE ANHYDROUS; OLIVE OIL; Phenoxyethanol; Polyglyceryl-2 Dipolyhydroxystearate; Polyglyceryl-3 Diisostearate; Potassium Sorbate; ALMOND OIL; Sodium Benzoate; Tocopherol; Water

Pure Baby Diaper Rash Cream

Drug Facts

Active Ingredients

Zinc Oxide 12%

Purpose

Skin Protectant

Uses

- Helps treat and prevent diaper rash
- Protects chafed skin due to diaper rash and helps seal out wetness.

Warnings

For external use only.

When using this product avoid contact with the eyes.

Stop use and ask a doctor if condition worsens or lasts more than 7 days.

Keep out of reach of children. If swallowed, get medical help or contact a Poison Control Center right away.

Directions

- Change wet and solid diapers promptly
- Clean the diaper area and allow to dry
- Apply cream liberally as often as necessary, with each diaper change, especially at bedtime or anytime when exposure to wet diaper may be prolonged.

Inactive Ingredients

Bisabolol, Calendula Officinalis Flower Extract, Caprylic/Capric Triglyceride, Coco-Caprylate, Dunaliella Salina Extract, Ethylhexylglycerin, Globularia Alypum Leaf Extract, Glycerin, Helianthus Annuus (Sunflower) Seed Oil, Hydrogenated Castor Oil, Magnesium Sulfate, Olea Europaea (Olive) Fruit Oil, Phenoxyethanol, Polyglyceryl-2 Dipolyhydroxystearate, Polyglyceryl-3 Diisostearate, Potassium Sorbate, Prunus Amygdalus Dulcis (Sweet Almond) Oil, Sodium Benzoate, Tocopherol, Water.

Questions or Comments?

Call 1-888-553-6112 Mon-Fri

Manufactured by:
Fischer Pharmaceuticals Ltd.
Tel Aviv, POB 39071, Israel.

PRINCIPAL DISPLAY PANEL - 113 g Tube Label

Dr. Fischer®

Pure
baby

Diaper Rash Cream

100%
ORGANIC OILS

Helps Treat &
Prevent

With
Natural
Origin Ingredients

SCIENCE INSIDE
- SCIENCE INSIDE -

Hypoallergenic • Sensitive Tested

NO
Fragrance, Parabens, SLS, SLES,
Lanolin, Silicones, Paraffin, GMOs

Net Wt. 4 oz. (113 g.)

FISCHER PHARMACEUTICALS